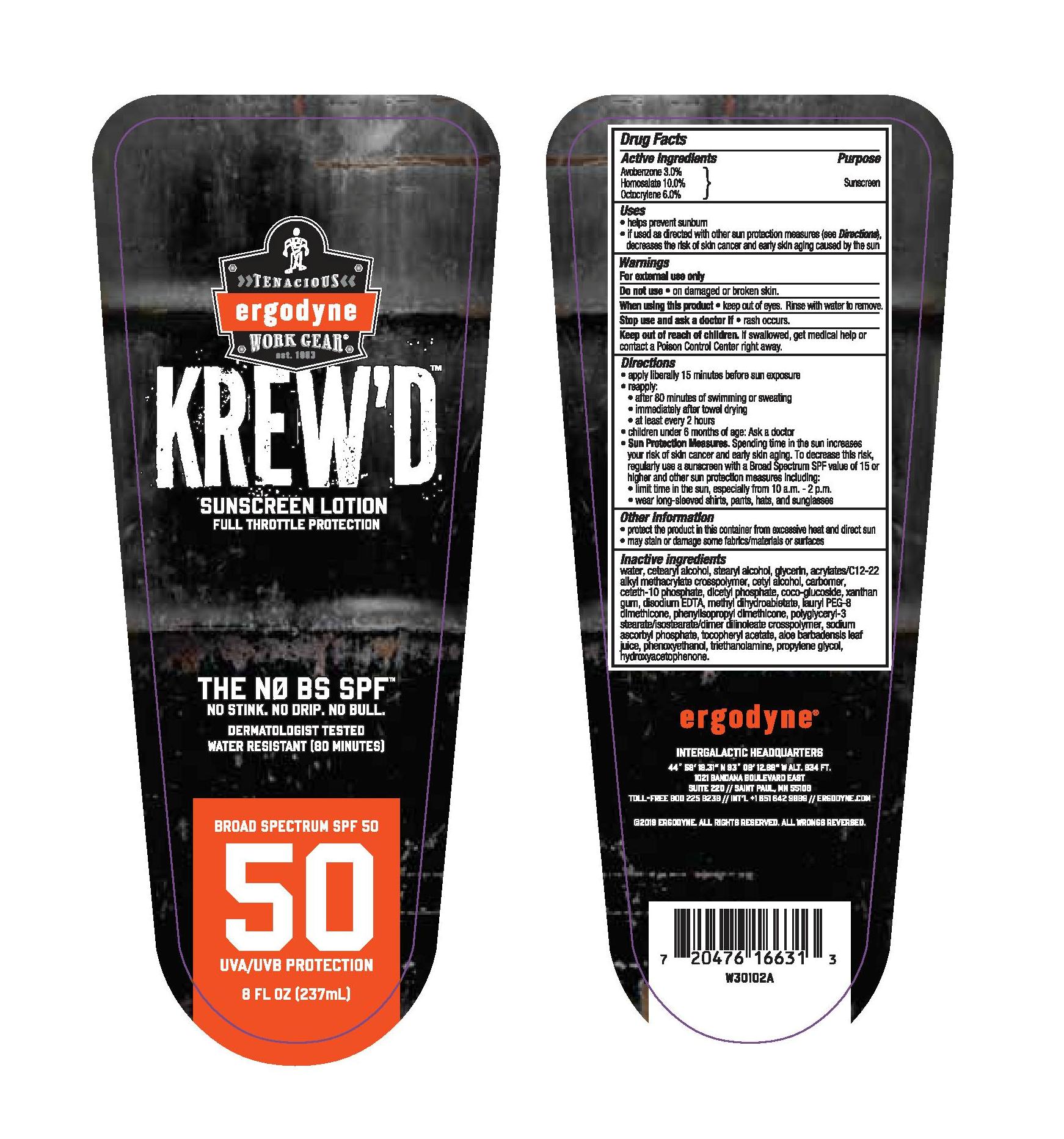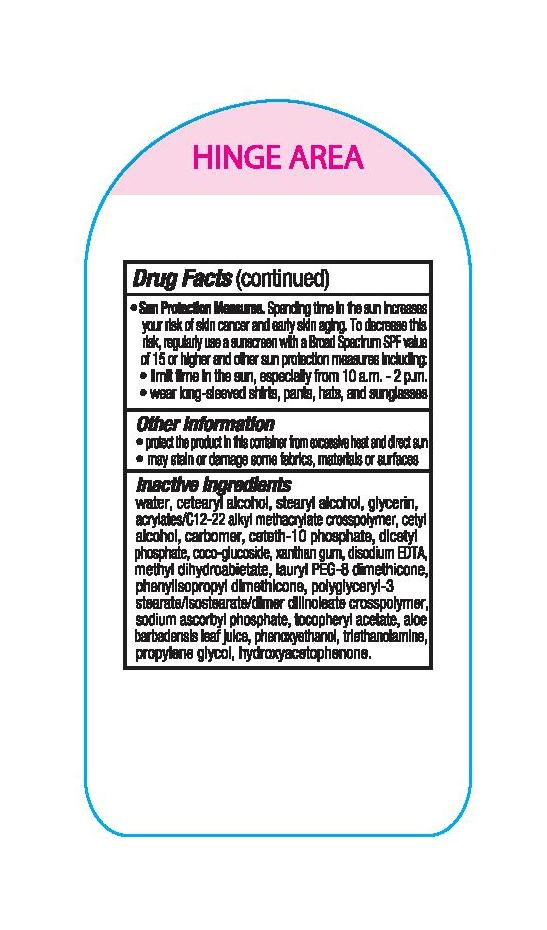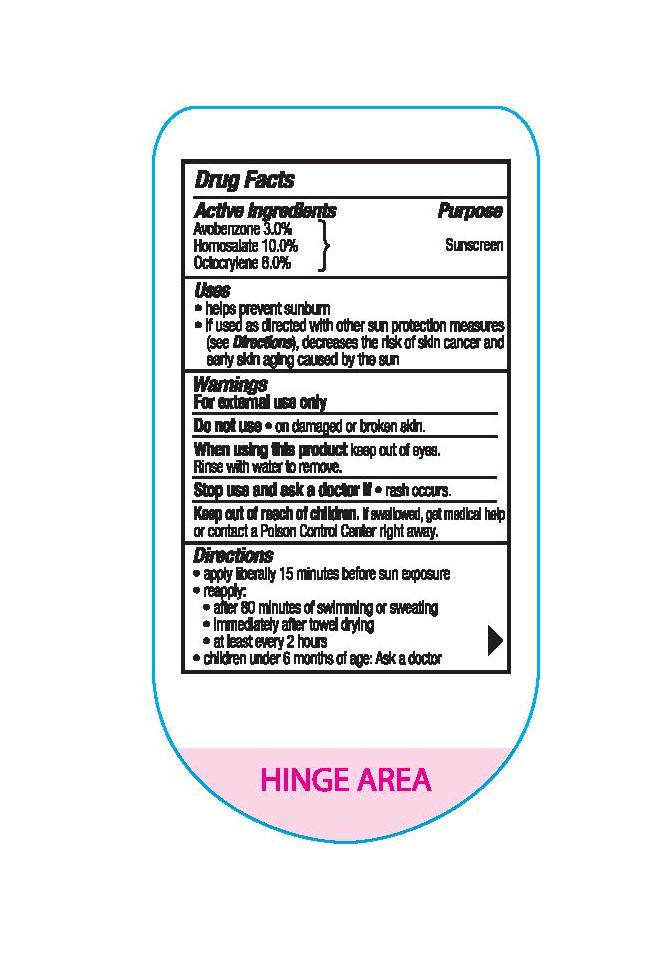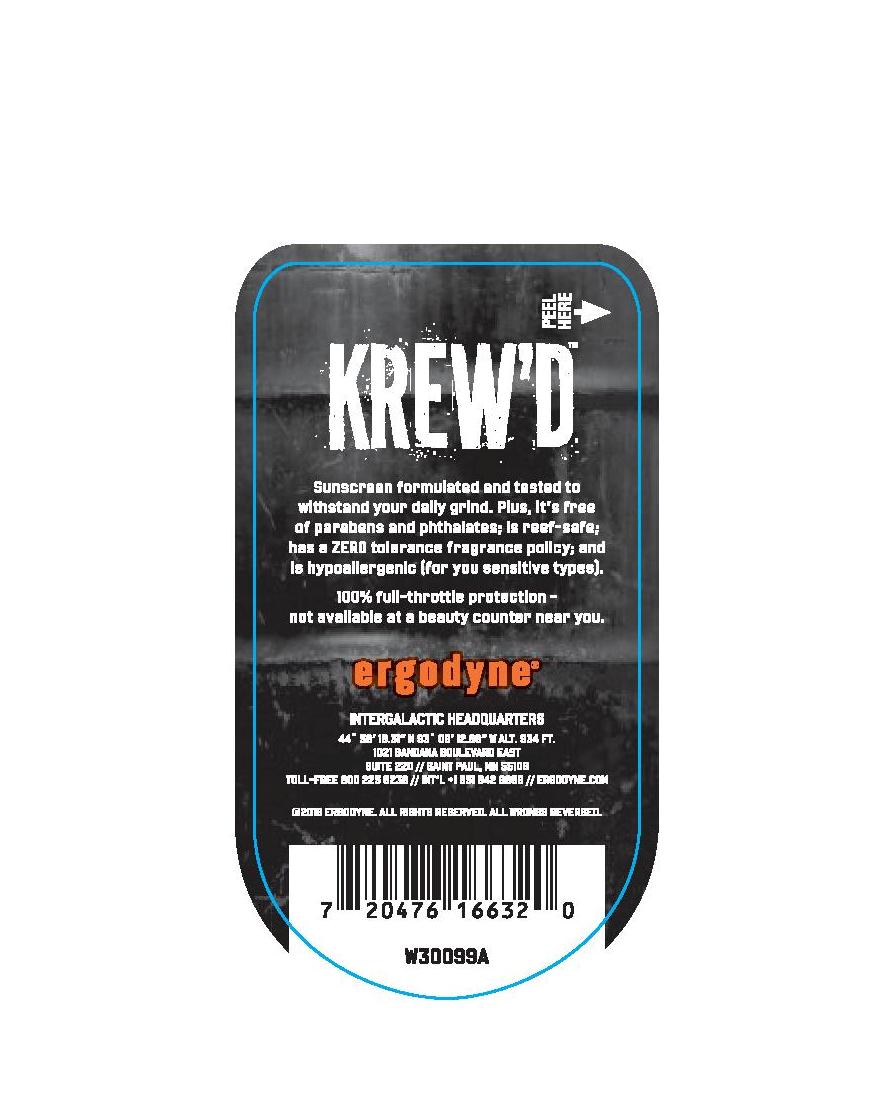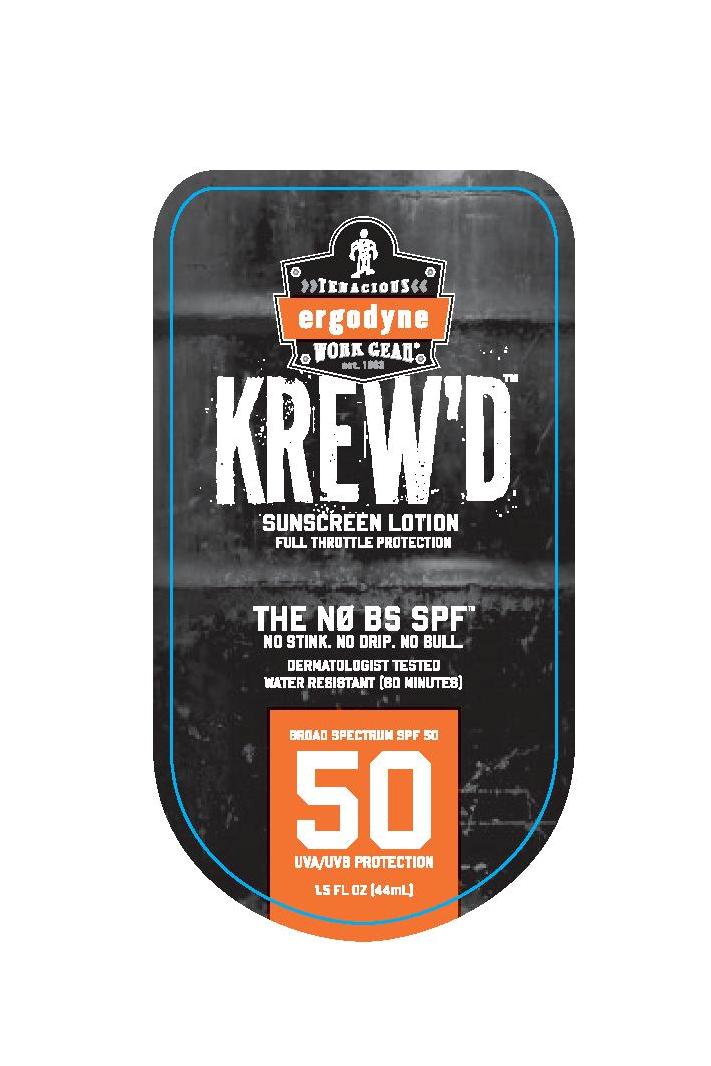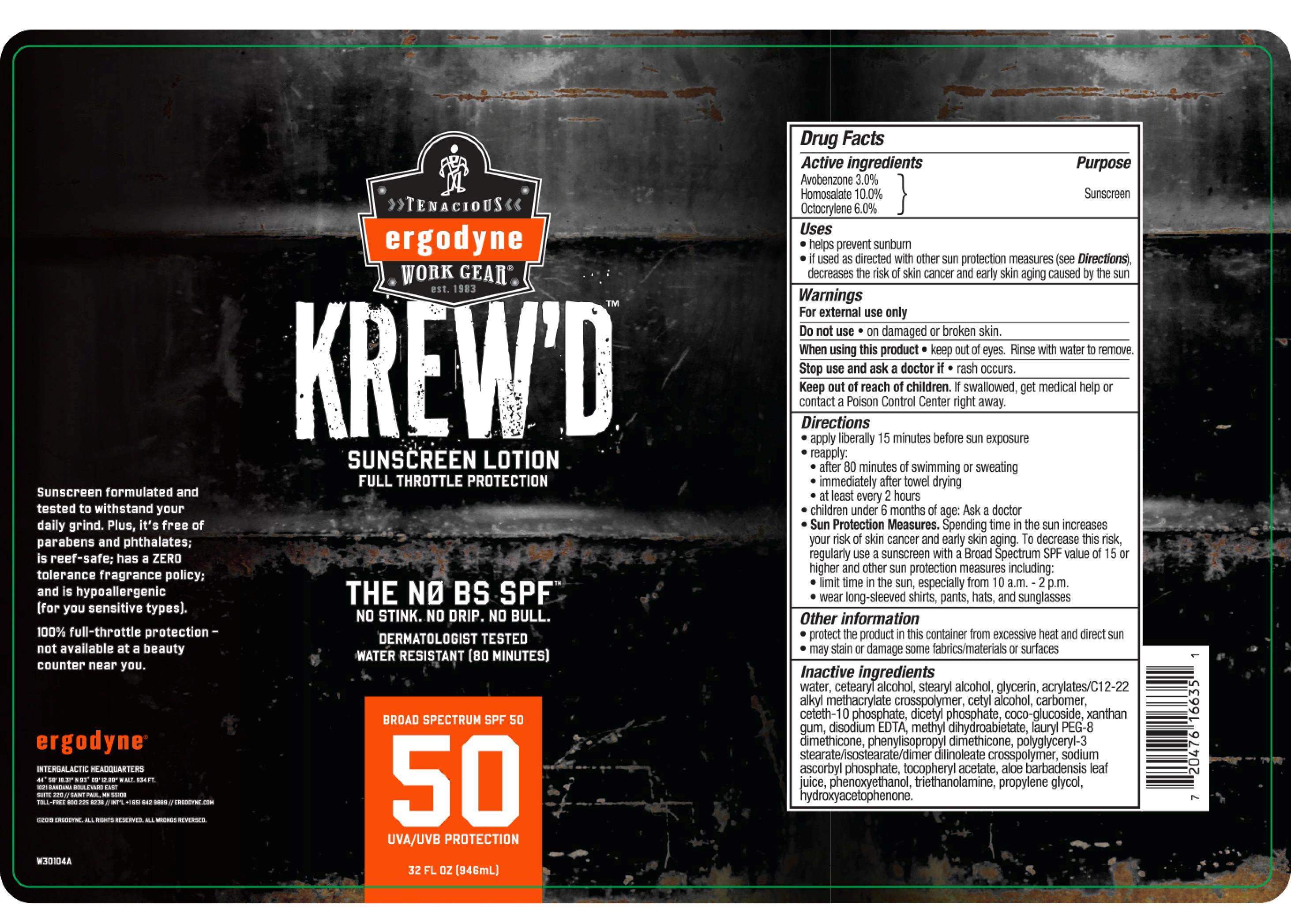 DRUG LABEL: Tenacious
NDC: 73620-001 | Form: LOTION
Manufacturer: Tenacious Holdings, Inc.
Category: otc | Type: HUMAN OTC DRUG LABEL
Date: 20241023

ACTIVE INGREDIENTS: HOMOSALATE 100 mg/1 mL; OCTOCRYLENE 60 mg/1 mL; AVOBENZONE 30 mg/1 mL
INACTIVE INGREDIENTS: WATER; CETOSTEARYL ALCOHOL; STEARYL ALCOHOL; GLYCERIN; BUTYL ACRYLATE/C16-C20 ALKYL METHACRYLATE/METHACRYLIC ACID/METHYL METHACRYLATE COPOLYMER; CETYL ALCOHOL; CARBOMER HOMOPOLYMER TYPE C; CETETH-10 PHOSPHATE; DIHEXADECYL PHOSPHATE; COCO GLUCOSIDE; XANTHAN GUM; EDETATE DISODIUM; METHYL DIHYDROABIETATE; SODIUM ASCORBYL PHOSPHATE; .ALPHA.-TOCOPHEROL ACETATE; ALOE VERA LEAF; PHENOXYETHANOL; TROLAMINE; PROPYLENE GLYCOL; HYDROXYACETOPHENONE

Tenacious Ergodyne SPF 50 Sunscreen Lotion

Active ingredients

Avobenzone 3.0%, Homosalate 10.0%, Octocrylene 6.0%

Purpose

Sunscreen

Uses

- helps prevent sunburn
- if used as directed with other sun protection measures (see Directions), decreases the risk of skin cancer and early skin aging caused by the sun

Warnings

For external use only

Do not use

• on damaged or broken skin.

When using this product

• keep out of eyes. Rinse with water to remove.

Stop use and ask a doctor if

• rash occurs.

Keep out of reach of children.

If swallowed, get medical help or contact a Poison Control Center right away.

Directions

- apply liberally 15 minutes before sun exposure
- reapply:

• after 80 minutes of swimming or sweating

• immediately after towel drying

• at least every 2 hours

- children under 6 months of age: Ask a doctor
- Sun Protection Measures. Spending time in the sun increases your risk of skin cancer and early skin aging. To decrease this risk, regularly use a sunscreen with a Broad Spectrum SPF value of 15 or higher and other sun protection measures including:

• limit time in the sun, especially from 10 a.m.-2 p.m.

• wear long-sleeved shirts, pants, hats, and sunglasses

Other information

- protect the product in this container from excessive heat and direct sun
- may stain or damage some fabrics/materials or surfaces

Inactive ingredients

water, cetearyl alcohol, stearyl alcohol, glycerin, acrylates/C12-22 alkyl methacrylate crosspolymer, cetyl alcohol, carbomer, ceteth-10 phosphate, dicetyl phosphate, coco-glucoside, xanthan gum, disodium EDTA, methyl dihydroabietate, lauryl PEG-8 dimethicone, phenylisopropyl dimethicone, polyglyceryl-3 stearate/isostearate/dimer dilinoleate crosspolymer, sodium ascorbyl phosphate, tocopheryl acetate, aloe barbadensis leaf juice, phenoxyethanol, triethanolamine, propylene glycol, hydroxyacetophenone.

PACKAGE LABEL

Tenacious Ergodyne SPF 50 Lotion

8 FL OZ (237mL)

NDC 73620-001-11

Tenacious Ergodyne SPF 50 Lotion

1.5 OZ (44mL)

NDC 73620-001-49

Tenacious Ergodyne SPF 50 Lotion

32 FL OZ (946mL)

NDC 73620-001-72